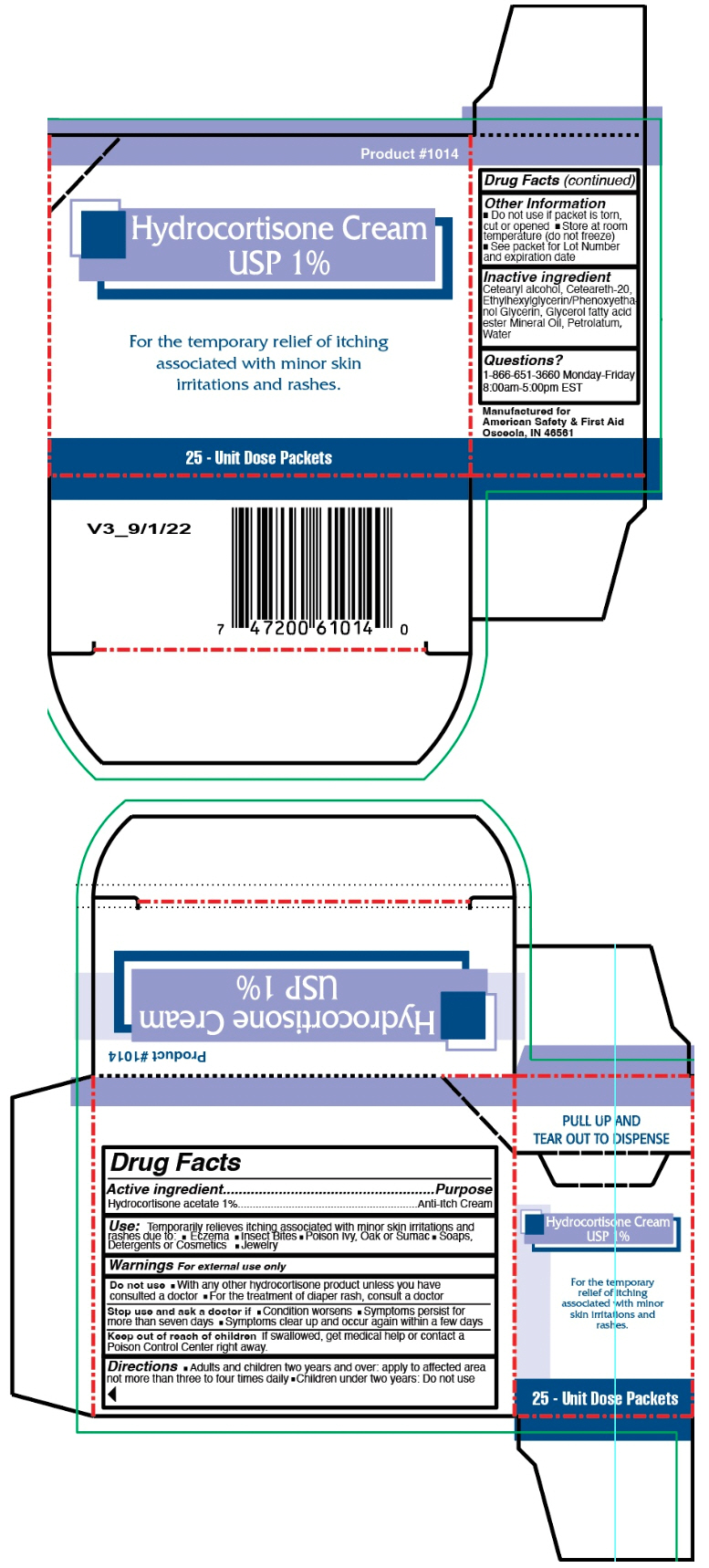 DRUG LABEL: HYDROCORTISONE
NDC: 73598-1014 | Form: CREAM
Manufacturer: JHK Inc dba American Safety & First Aid
Category: otc | Type: HUMAN OTC DRUG LABEL
Date: 20240425

ACTIVE INGREDIENTS: HYDROCORTISONE ACETATE 0.9 g/0.9 g
INACTIVE INGREDIENTS: CETOSTEARYL ALCOHOL; POLYOXYL 20 CETOSTEARYL ETHER; PETROLATUM; WATER

HYDROCORTISONE CREAM 1%

Drug Facts

Active ingredient

Hydrocortisone acetate 1%

Purpose

Anti-Itch Cream

Use

Temporarily relieves itching associated with minor skin irritations and rashes due to:

- Eczema
- Insect Bites
- Poison Ivy, Oak or Sumac
- Soaps, Detergents or Cosmetics
- Jewelry

Warnings

For external use only

Do not use

- With any other hydrocortisone product unless you have consulted a doctor
- For the treatment of diaper rash, consult a doctor

Stop use and ask a doctor if

- Condition worsens
- Symptoms persist for more than seven days
- Symptoms clear up and occur again within a few days

Keep out of reach of children

If swallowed, get medical help or contact a Poison Control Center right away.

Directions

- Adults and children two years and over: apply to affected area not more than three to four times daily
- Children under two years: Do not use

Other Information

- Do not use if packet is torn, cut or opened
- Store at room temperature (do not freeze)
- See packet for Lot Number and expiration date

Inactive ingredient

Cetearyl alcohol, Ceteareth-20, Ethylhexylglycerin/Phenoxyethanol Glycerin, Glycerol fatty acid ester Mineral Oil, Petrolatum, Water

Questions?

1-866-651-3660 Monday-Friday

8:00am-5:00pm EST

PRINCIPAL DISPLAY PANEL - 25 Packet Carton

Product #1014

Hydrocortisone Cream
USP 1%

For the temporary relief of itching
associated with minor skin
irritations and rashes.

25 - Unit Dose Packets